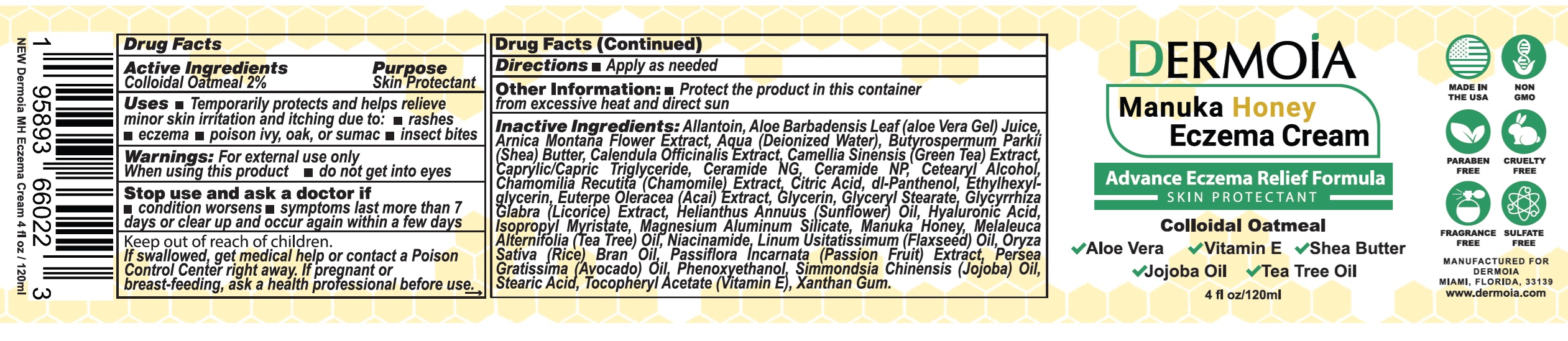 DRUG LABEL: Dermoia Manuka Honey Eczema
NDC: 83524-607 | Form: CREAM
Manufacturer: TREASUREWISE LLC
Category: otc | Type: HUMAN OTC DRUG LABEL
Date: 20250115

ACTIVE INGREDIENTS: OATMEAL 20 mg/1 mL
INACTIVE INGREDIENTS: ALLANTOIN; ALOE VERA LEAF; ARNICA MONTANA FLOWER; WATER; SHEA BUTTER; CALENDULA OFFICINALIS FLOWER; GREEN TEA LEAF; MEDIUM-CHAIN TRIGLYCERIDES; CERAMIDE NG; CERAMIDE NP; CETOSTEARYL ALCOHOL; CHAMOMILE; CITRIC ACID MONOHYDRATE; PANTHENOL; ETHYLHEXYLGLYCERIN; ACAI; GLYCERIN; GLYCERYL MONOSTEARATE; GLYCYRRHIZA GLABRA; HELIANTHUS ANNUUS FLOWERING TOP; HYALURONIC ACID; ISOPROPYL MYRISTATE; MAGNESIUM ALUMINUM SILICATE; TEA TREE OIL; NIACINAMIDE; FLAX SEED; RICE BRAN OIL; AVOCADO OIL; PHENOXYETHANOL; JOJOBA OIL; STEARIC ACID; .ALPHA.-TOCOPHEROL ACETATE; XANTHAN GUM

Dermoia Manuka Honey Eczema Cream

Active Ingredients

Colloidal Oatmeal 2%

Purpose

Skin Protectant

Uses

- Temporarily protects and helps relieve minor skin irritation and itching due to:
- rashes
- eczema
- poison ivy, oak, or sumac
- insect bites

Warnings:

For external use only

When using this product

- do not get into eyes

Stop use and ask a doctor if

- condition worsens
- symptoms last more than 7 days or clear up and occur again within a few days

Keep out of reach of children.

If swallowed, get medical help or contact a Poison Control Center right away.

If pregnant or breast-feeding,

askahealthprofessionalbeforeuse.

Directions

- Apply as needed

Other Information:

- Protect the product in this container from excessive heat and direct sun

Inactive Ingredients:

Allantoin, Aloe Barbadensis Leaf (aloe Vera Gel) Juice, Arnica Montana Flower Extract, Aqua (Deionized Water), Butyrospermum Parkii (Shea) Butter, Calendula Officinalis Extract, Camellia Sinensis (Green Tea) Extract, Caprylic/Capric Triglyceride, Ceramide NG, Ceramide NP, Cetearyl Alcohol, Chamomilia Recutita (Chamomile) Extract, Citric Acid, dl-Panthenol, Ethylhexyl- glycerin, Euterpe Oleracea (Acai) Extract, Glycerin, Glyceryl Stearate, Glycyrrhiza Glabra (Licorice) Extract, Helianthus Annuus (Sunflower) Oil, Hyaluronic Acid, Isopropyl Myristate, Magnesium Aluminum Silicate, Manuka Honey, Melaleuca Alternifolia (Tea Tree) Oil, Niacinamide, Linum Usitatissimum (Flaxseed) Oil, Oryza Sativa (Rice) Bran Oil, Passiflora Incarnata (Passion Fruit) Extract, Persea Gratissima (Avocado) Oil, Phenoxyethanol, Simmondsia Chinensis (Jojoba) Oil, Stearic Acid, Tocopheryl Acetate (Vitamin E), Xanthan Gum.